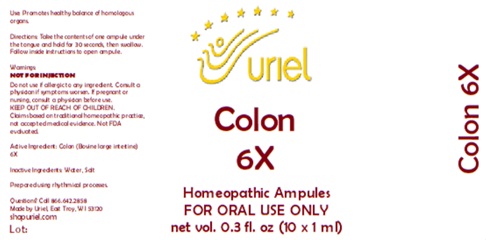 DRUG LABEL: Colon 6
NDC: 48951-3114 | Form: LIQUID
Manufacturer: Uriel Pharmacy Inc.
Category: homeopathic | Type: HUMAN OTC DRUG LABEL
Date: 20260203

ACTIVE INGREDIENTS: BOS TAURUS COLON 6 [hp_X]/1 mL
INACTIVE INGREDIENTS: WATER; SODIUM CHLORIDE

Colon 6

PURPOSE

Use: Promotes healthy balance of homologous organs.

INDICATIONS AND USAGE

FOR ORAL USE ONLY

DOSAGE AND ADMINISTRATION

Directions: Take the contents of one ampule under the tongue and hold for 30 seconds, then swallow. Follow inside instructions to open ampule.

Warnings:
NOT FOR INJECTION
Do not use if allergic to any ingredient. Consult a physician if symptoms worsen. If pregnant or nursing, consult a physician before use.
Claims based on traditional homeopathic practice, not accepted medical evidence. Not FDA evaluated

KEEP OUT OF REACH OF CHILDREN.

Active Ingredient: Colon (Bovine large intestine) 6X

Inactive Ingredients: Water, Salt

Prepared using rhythmical processes.

Questions? Call 866.642.2858
Made by Uriel, East Troy, WI 53120
shopuriel.com

Lot: